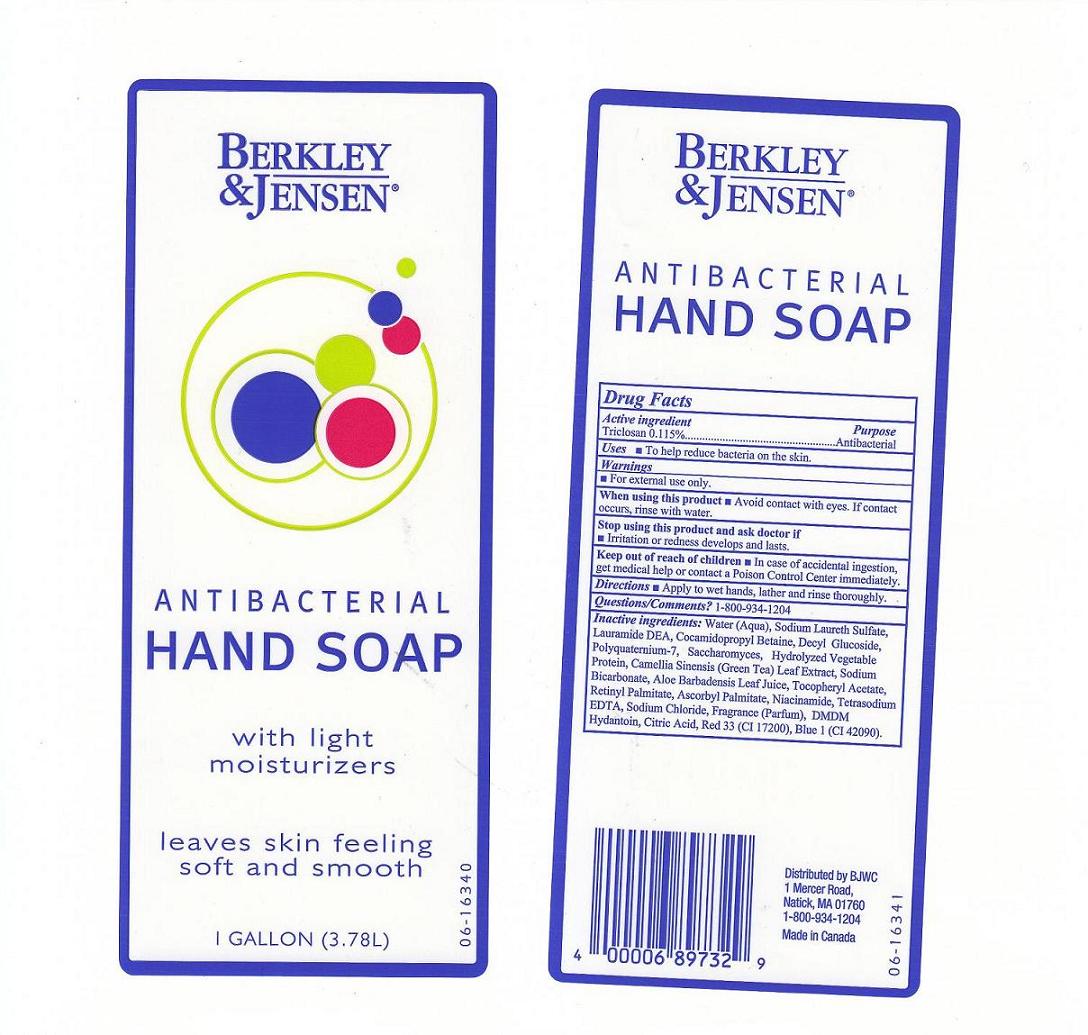 DRUG LABEL: ANTIBACTERIAL 
NDC: 68391-141 | Form: SOAP
Manufacturer: BJWC
Category: otc | Type: HUMAN OTC DRUG LABEL
Date: 20100723

ACTIVE INGREDIENTS: TRICLOSAN 0.115 mL/100 mL
INACTIVE INGREDIENTS: WATER; SODIUM LAURETH SULFATE; LAURIC DIETHANOLAMIDE; COCAMIDOPROPYL BETAINE; POLYQUATERNIUM-7 (70/30 ACRYLAMIDE/DADMAC; 1600 KD); SACCHAROMYCES CEREVISIAE; GREEN TEA LEAF; SODIUM BICARBONATE; ALOE VERA LEAF; ALPHA-TOCOPHEROL ACETATE; VITAMIN A PALMITATE; ASCORBYL PALMITATE; NIACINAMIDE; EDETATE SODIUM; SODIUM CHLORIDE; DMDM HYDANTOIN; CITRIC ACID MONOHYDRATE; D&C RED NO. 33; FD&C BLUE NO. 1

Drug Facts Box - Back Label

Active Ingredient

Triclosan 0.115%

Purpose

- Antibacterial.

Warnings

For external use only.

When using this product

Avoid contact with eyes. If contact occurs, rinse with water.

Stop using this product and ask doctor if

Irritation or redness develops and lasts.

Keep out of reach of children

In case of accidental ingestions, get medical help or contact a Poison Control Center immediately.

Questions/Comments?

1-800-934-1204

Directions

Apply to wet hands, lather and rinse thoroughly.

Uses

To help reduce bacteria on the skin

Inactive Ingredeints

Water (Aqua), Sodium Laureth Sulfate, Lauramide DEA, Cocamidopropyl Betaine, Decyl Glucoside, Polyquaternium-7, Saccharomyces, Hydrolyzed Vegetable Protein, Camellia Sinensis (Green Tea) Leaf Extract, Sodium Bicarbonate, Aloe Barbadensis Leaf Juice, Tocopheryl Acetate, Retinyl Palmitate, Ascorbyl Palmitate, Niacinamide, Tetrasodium EDTA, Sodium Chloride, Fragrance (Parfum), DMDM Hydantoin, Citric Acid, Red 33 (CI 17200), Blue 1 (CI 42090).

Package Front and Back Labels

bj1g.jpg